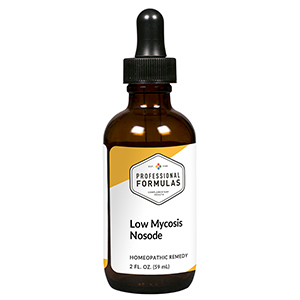 DRUG LABEL: Low Mycosis Nosode
NDC: 63083-4021 | Form: LIQUID
Manufacturer: Professional Complementary Health Formulas
Category: homeopathic | Type: HUMAN OTC DRUG LABEL
Date: 20190815

ACTIVE INGREDIENTS: CANDIDA ALBICANS 12 [hp_X]/59 mL; CANDIDA TORRESII 12 [hp_X]/59 mL; CANDIDA TROPICALIS 12 [hp_X]/59 mL; PLEOSPORA HERBARUM 6 [hp_X]/59 mL; ASPERGILLUS NIGER VAR. NIGER 6 [hp_X]/59 mL; RHODOTORULA RUBRA 6 [hp_X]/59 mL; GEOTRICHUM CANDIDUM 6 [hp_X]/59 mL; MUCOR RACEMOSUS 6 [hp_X]/59 mL; PENICILLIN G 6 [hp_X]/59 mL; AUREOBASIDIUM PULLULANS VAR. PULLUTANS 6 [hp_X]/59 mL; RHIZOPUS STOLONIFER 6 [hp_X]/59 mL
INACTIVE INGREDIENTS: ALCOHOL; WATER

N21

ACTIVE INGREDIENTS

Candida albicans 12X
Candida torresii 12X
Candida tropicalis 12X
and all the following at 6X, 12X:
Alternaria
Aspergillus niger
Cryptococcus
Geotrichum candidum
Mucor racemosus
Penicillium notatum
Pullularia pullulans
Rhizopus nigricans

QUESTIONS

Professional Formulas

PO Box 2034 Lake Oswego, OR 97035

INDICATIONS

For the temporary relief of runny nose, sneezing, itching of the nose or throat, itchy or watery eyes, headache, chills, or irritated, red, or itchy skin.*

PURPOSE

*Claims based on traditional homeopathic practice, not accepted medical evidence. Not FDA evaluated.

WARNINGS

Persistent symptoms may be a sign of a serious condition. If symptoms persist or are accompanied by a fever, rash, or persistent headache, consult a doctor. Keep out of the reach of children. In case of overdose, get medical help or contact a poison control center right away. If pregnant or breastfeeding, ask a healthcare professional before use.

Keep out of the reach of children.

PREGNANCY OR BREAST FEEDING

If pregnant or breastfeeding, ask a healthcare professional before use.

DIRECTIONS

Place drops under tongue 30 minutes before/after meals. Adults and children 12 years and over: Take 10 to 15 drops once weekly or monthly. If mild symptoms are present, take 10 drops up to 3 times per day. Consult a physician for use in children under 12 years of age.

OTHER INFORMATION

Tamper resistant. If seal is broken, do not use. After opening, close container tightly and store at room temperature away from heat.

INACTIVE INGREDIENTS

20% ethanol, purified water.

LABEL

Est 1985

Professional Formulas

Complementary Health

Low Mycosis Nosode

Homeopathic Remedy

2 FL. OZ. (59 mL)